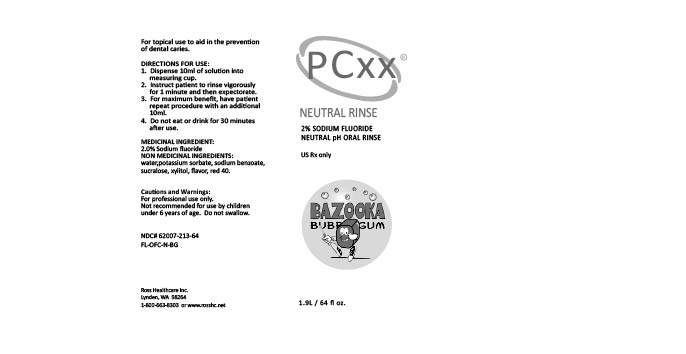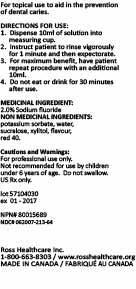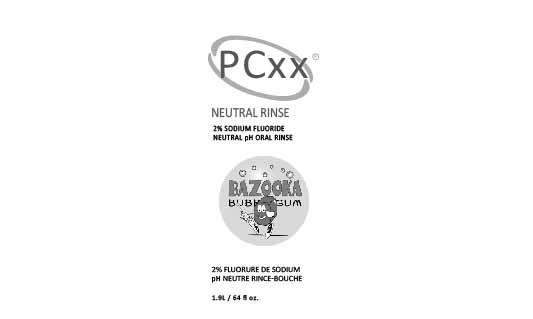 DRUG LABEL: PCXX NEUTRAL RMS BUBBLEGUM
NDC: 62007-213 | Form: RINSE
Manufacturer: Ross Healthcare Inc.
Category: prescription | Type: HUMAN PRESCRIPTION DRUG LABEL
Date: 20251106

ACTIVE INGREDIENTS: SODIUM FLUORIDE 20 mg/1 mL
INACTIVE INGREDIENTS: FD&C RED NO. 40 0.04 mg/1 mL

PCXX NEUTRAL RNS BUBBLEGUM